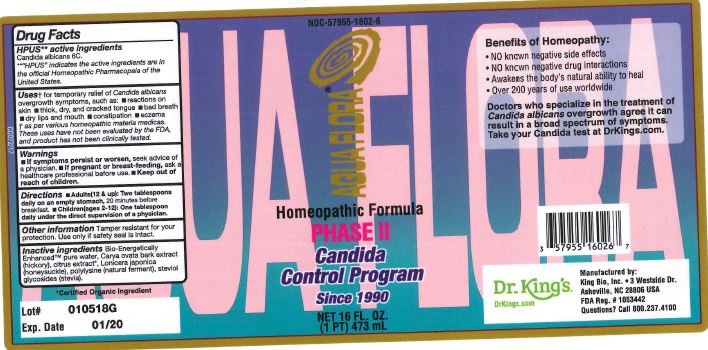 DRUG LABEL: Aquaflora Phase II
NDC: 57955-1602 | Form: LIQUID
Manufacturer: King Bio Inc
Category: homeopathic | Type: HUMAN OTC DRUG LABEL
Date: 20180403

ACTIVE INGREDIENTS: CANDIDA ALBICANS 6 [hp_C]/473 mL
INACTIVE INGREDIENTS: WATER; CARYA OVATA BARK; CITRUS BIOFLAVONOIDS; LONICERA JAPONICA FLOWER; POLYEPSILON-LYSINE (4000 MW); REBAUDIOSIDE A

Aquaflora Phase II

HPUS Active Ingredients

Candida albicans

Uses

for temporary relief of Candida albicans overgrowth symptoms, such as:

- reactions on skin
- thick, dry, and cracked tongue
- bad breath
- dry lips and mouth
- constipation
- eczema

Warnings

- If symptoms persist or worsen, seek advice of a physician.
- If pregnant or breast-feeding, ask a heathcare professional before use.

Keep out of reach of children

Directions

Adults(12 & up): Two tablespoons daily on an empty stoach, 20 minutes before breakfast

Children(ages 2-12): One tablespoon daily under the direct supervision of a physician.

Purpose

for temporary relief of Candida albicans

Other Information

Tamper resistant for your protection. Use only if safety seal is intact

Inactive Ingredients

Bio-Energetically Enhanced pure water, Carya ovata bark extract (hickory), citrus extract, Lonicera japonica (honeysuckle), polylysine (natural ferment), steviol glycosides (stevia)